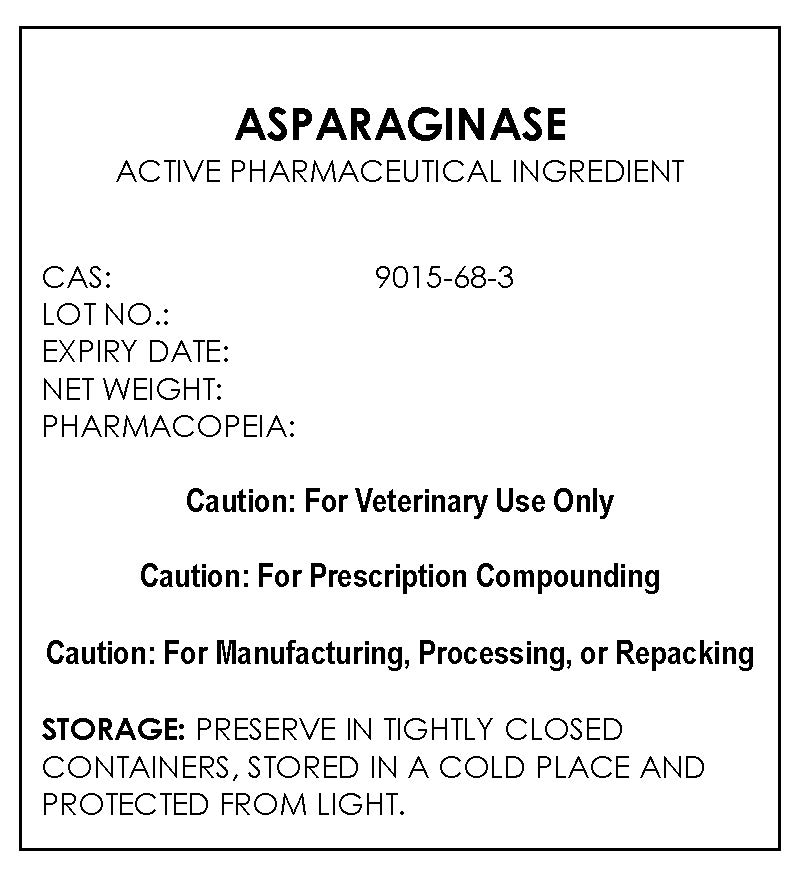 DRUG LABEL: ASPARAGINASE
NDC: 43744-020 | Form: POWDER
Manufacturer: CBSCHEM LIMITED
Category: other | Type: BULK INGREDIENT
Date: 20211209

ACTIVE INGREDIENTS: ASPARAGINASE 1 g/1 g

ASPARAGINASE

PACKAGE LABEL

asparaginaselabelfile.jpg